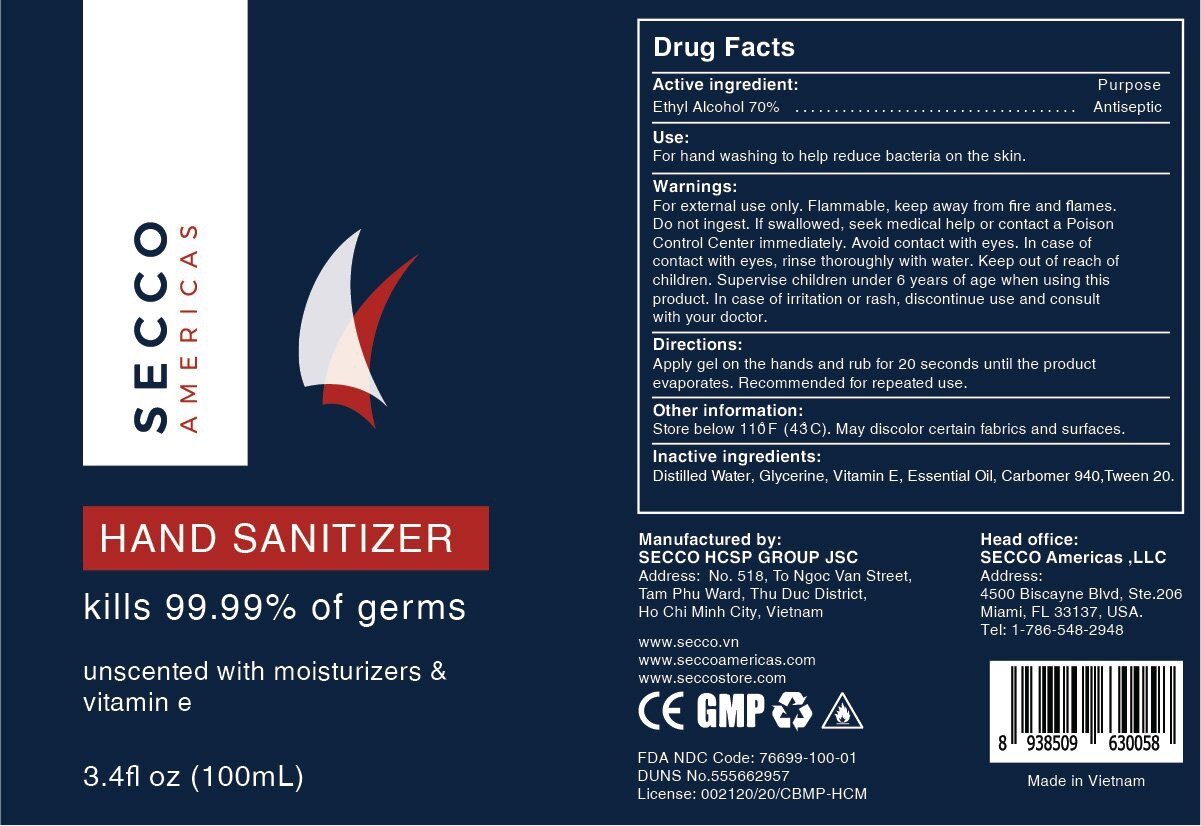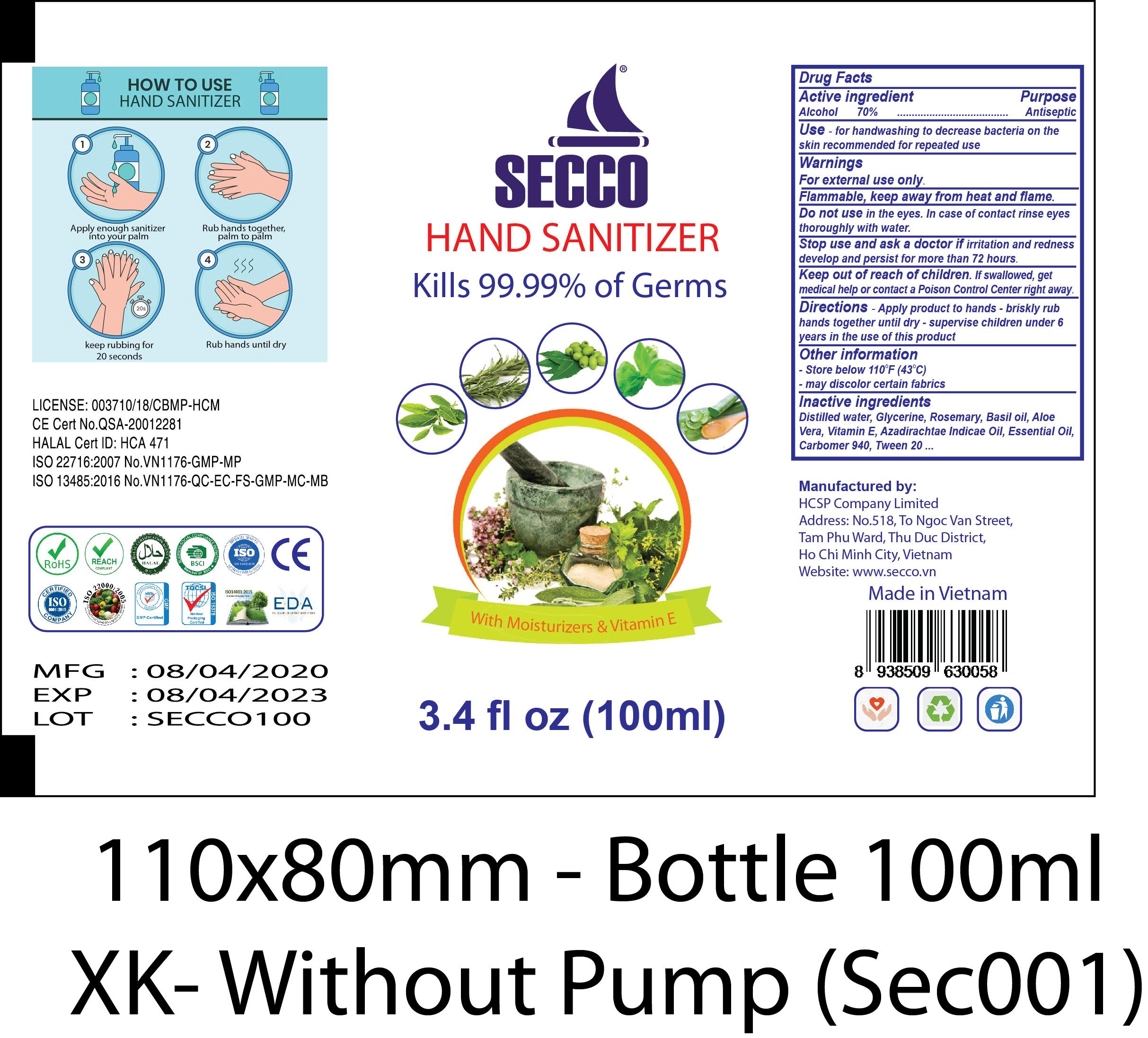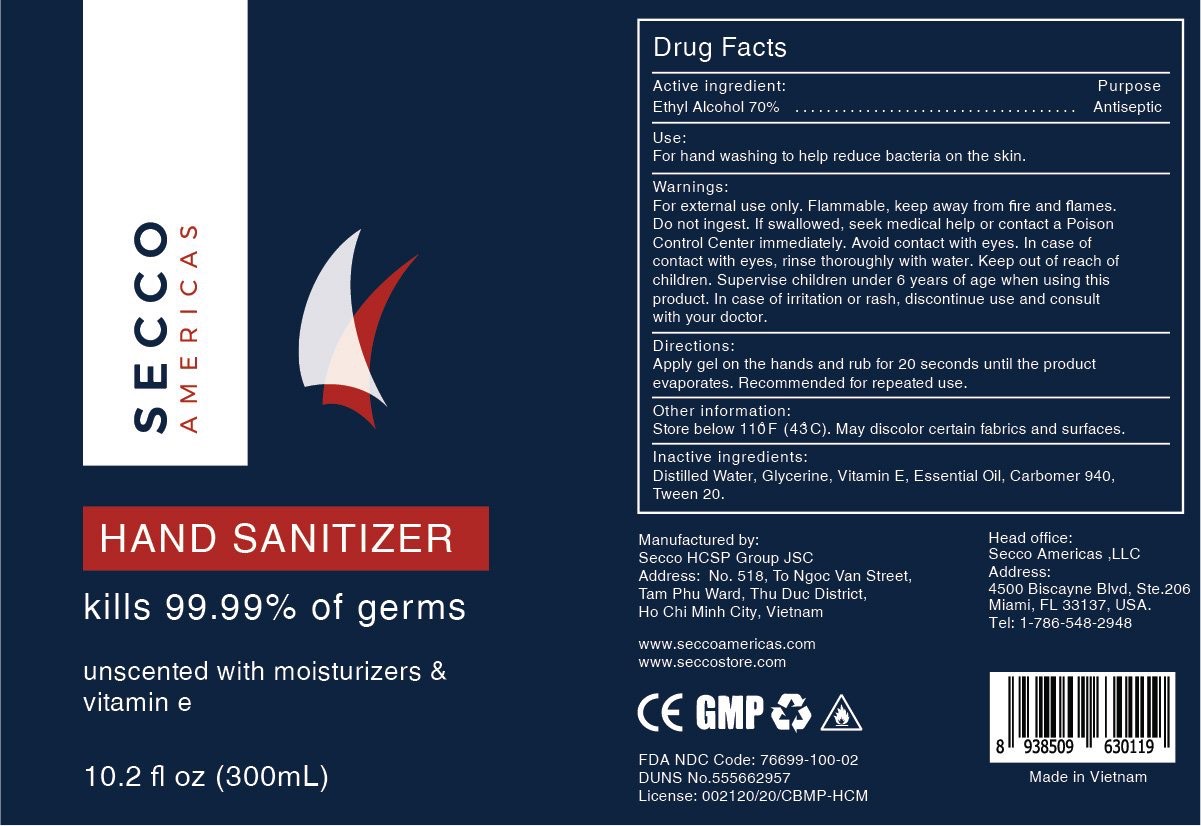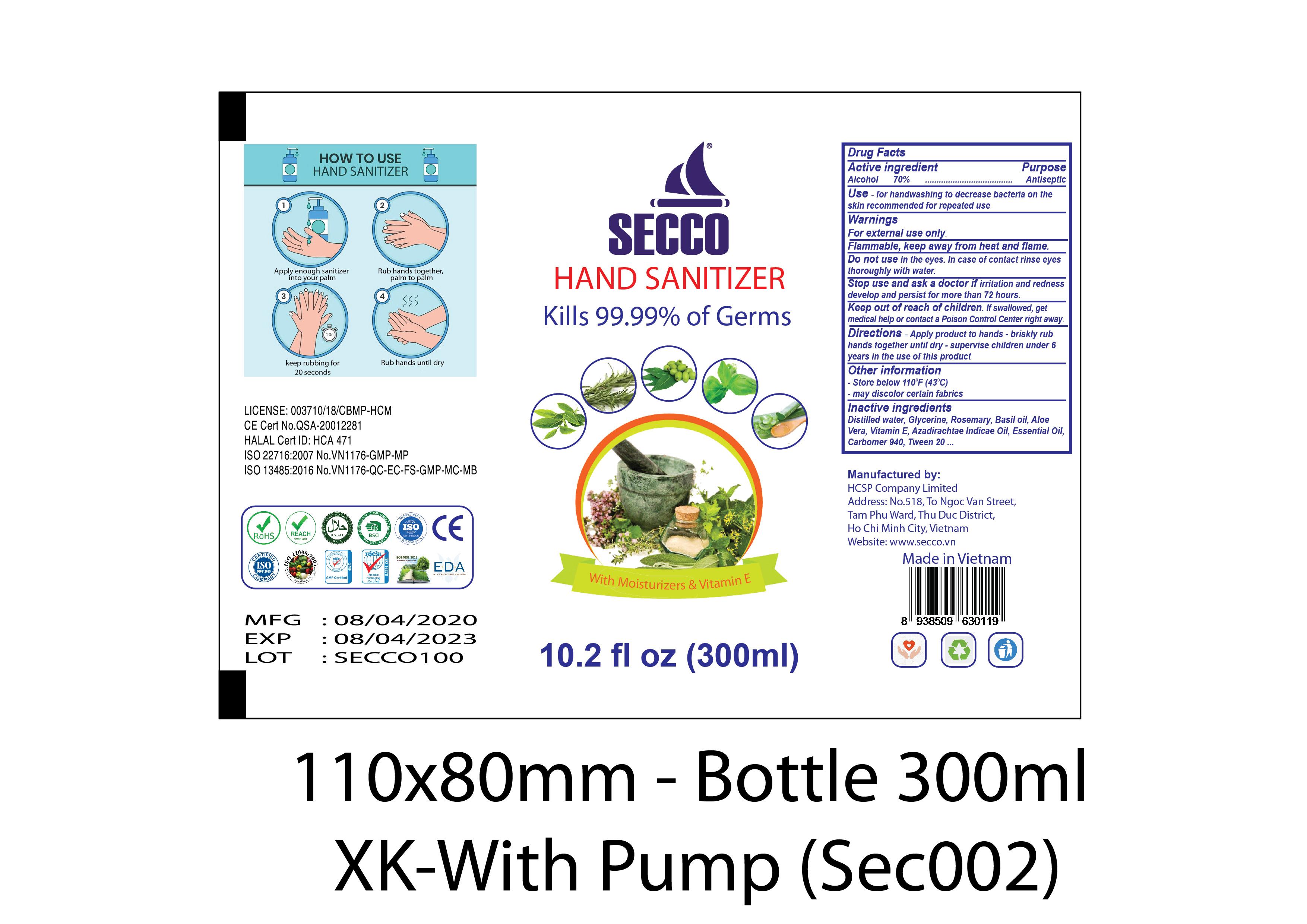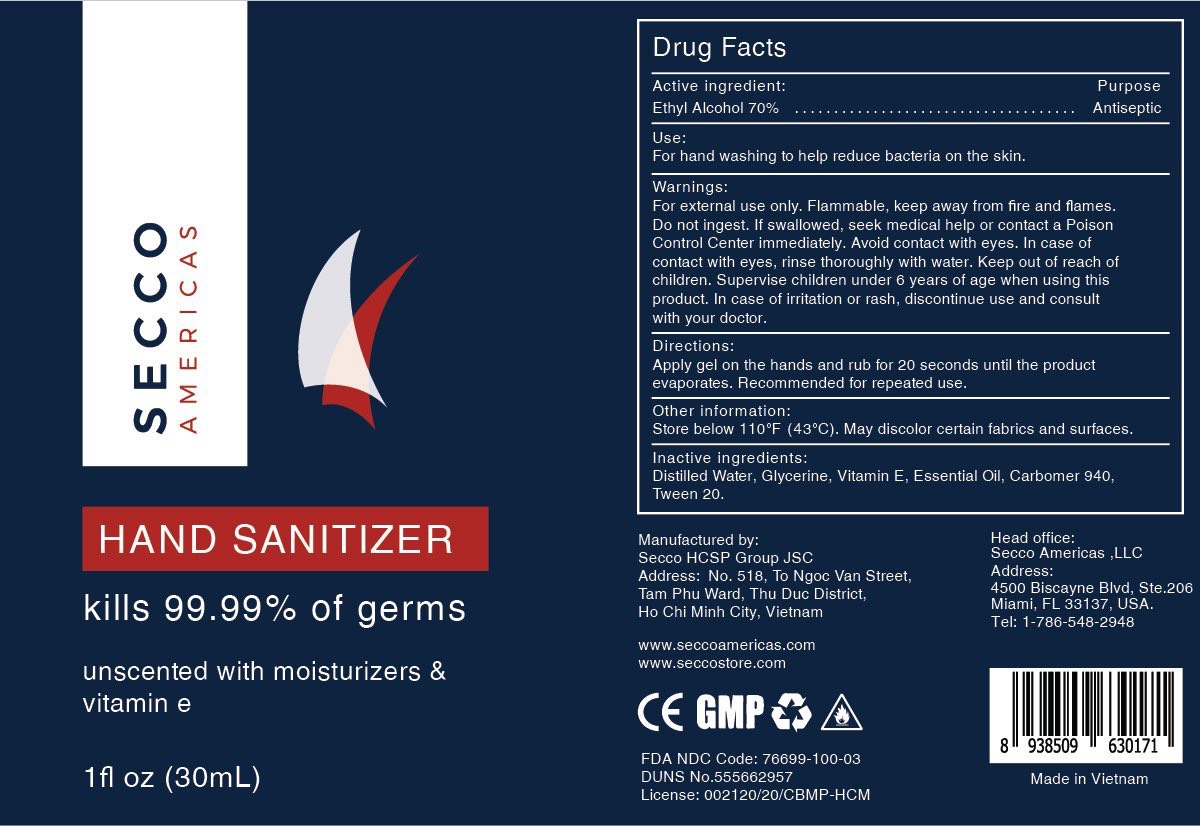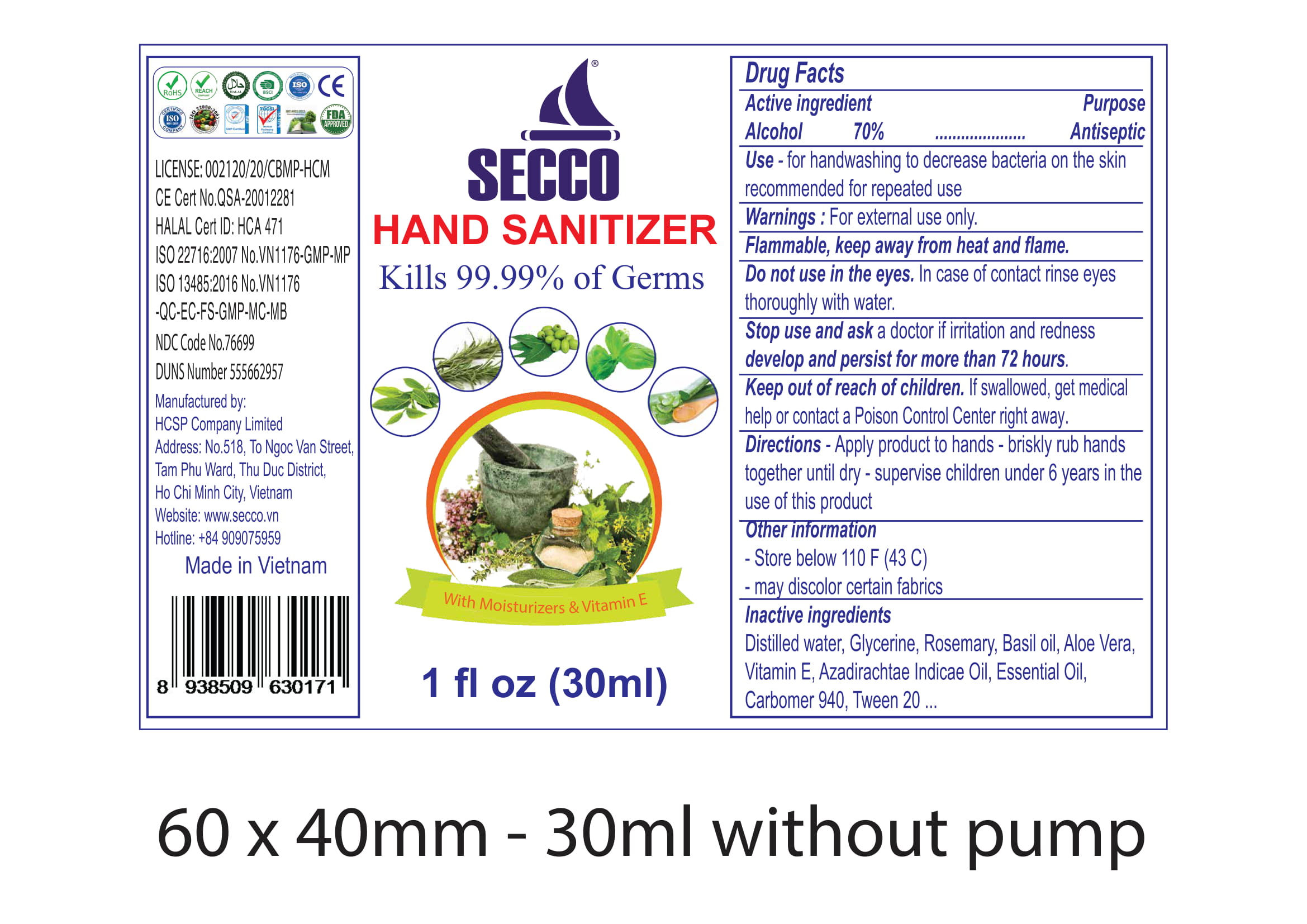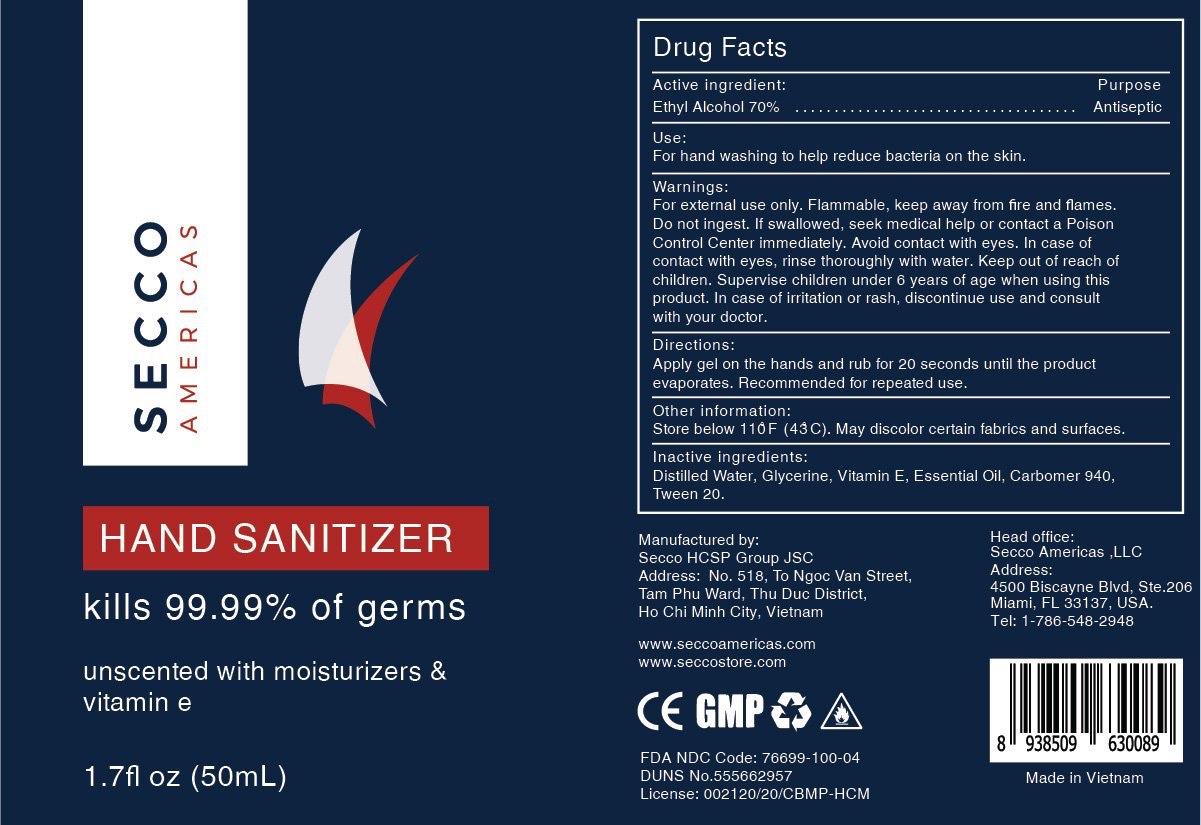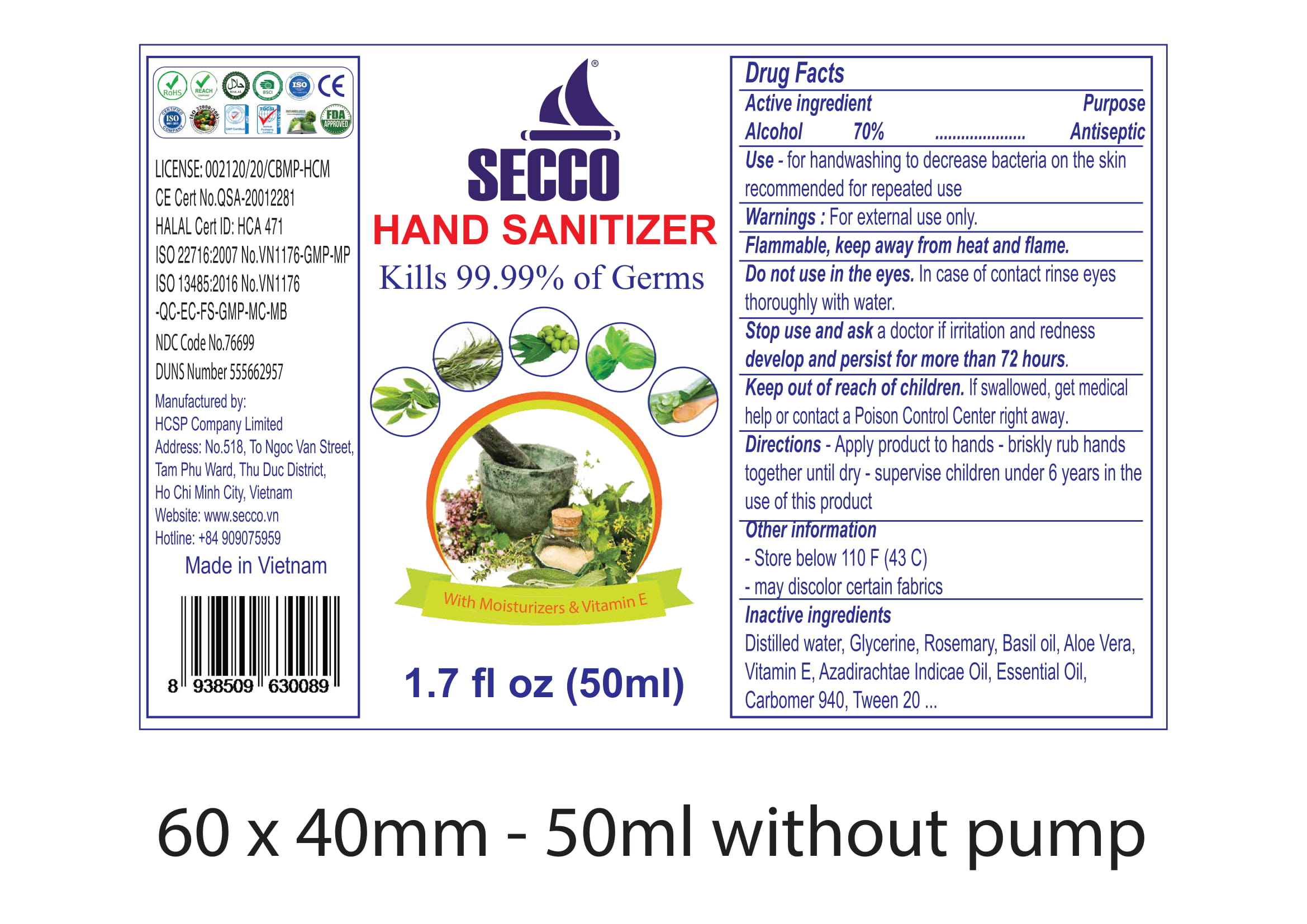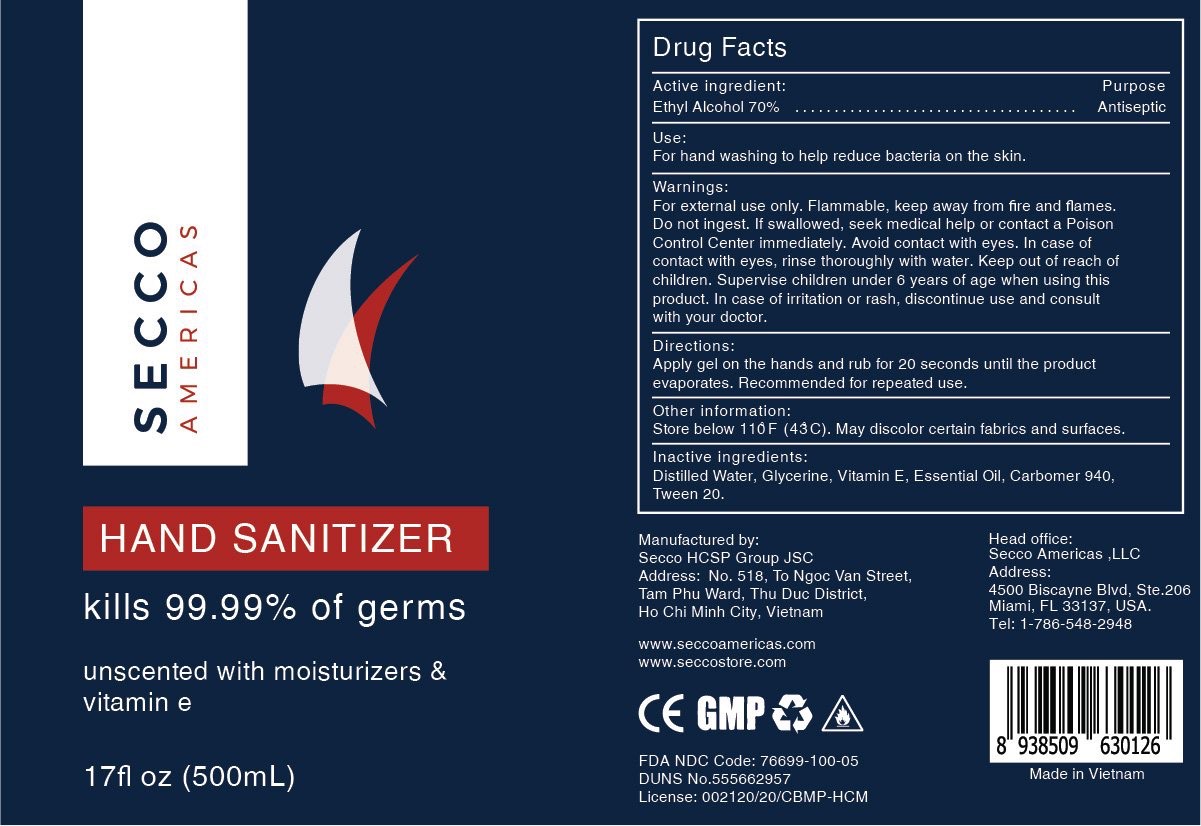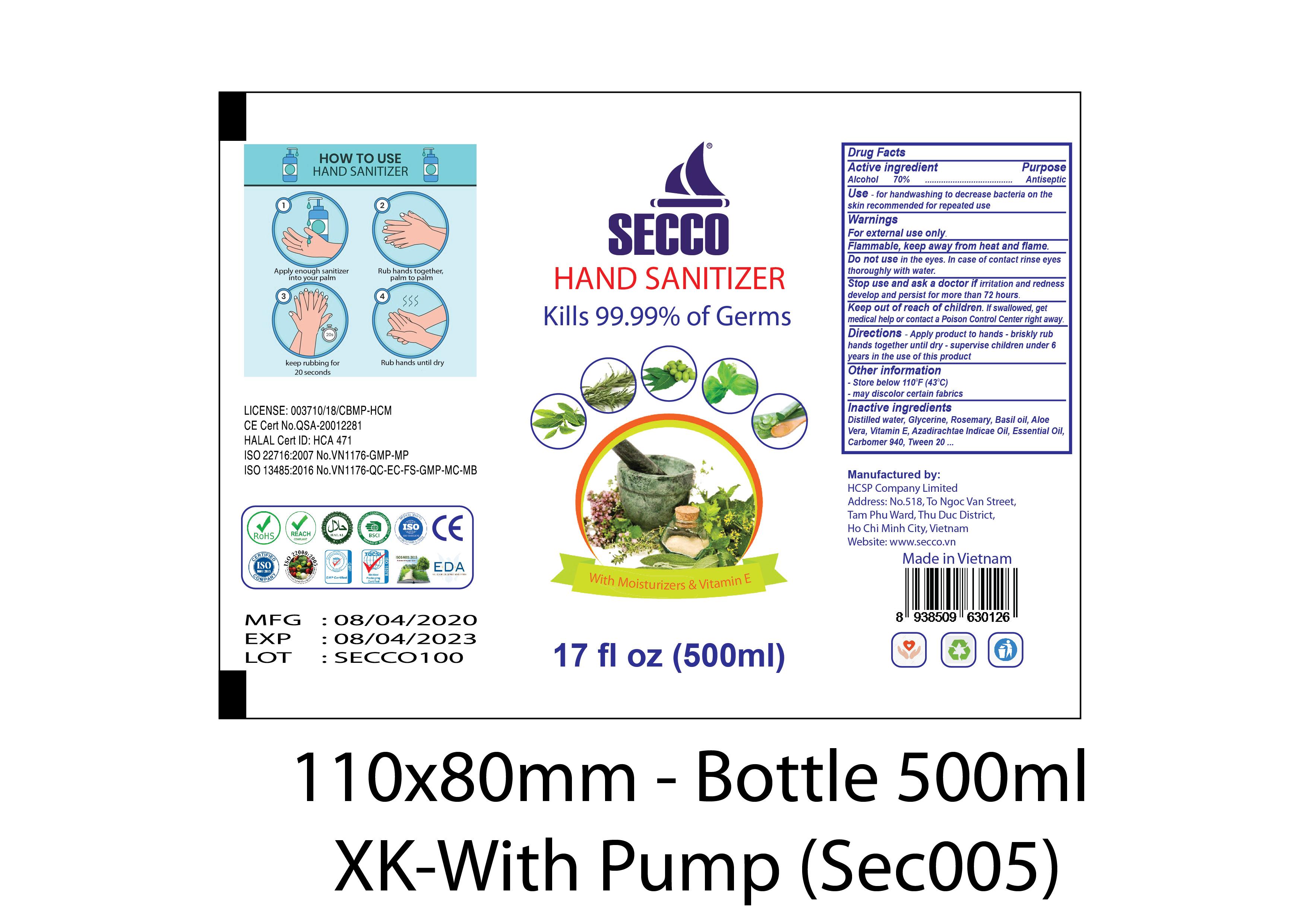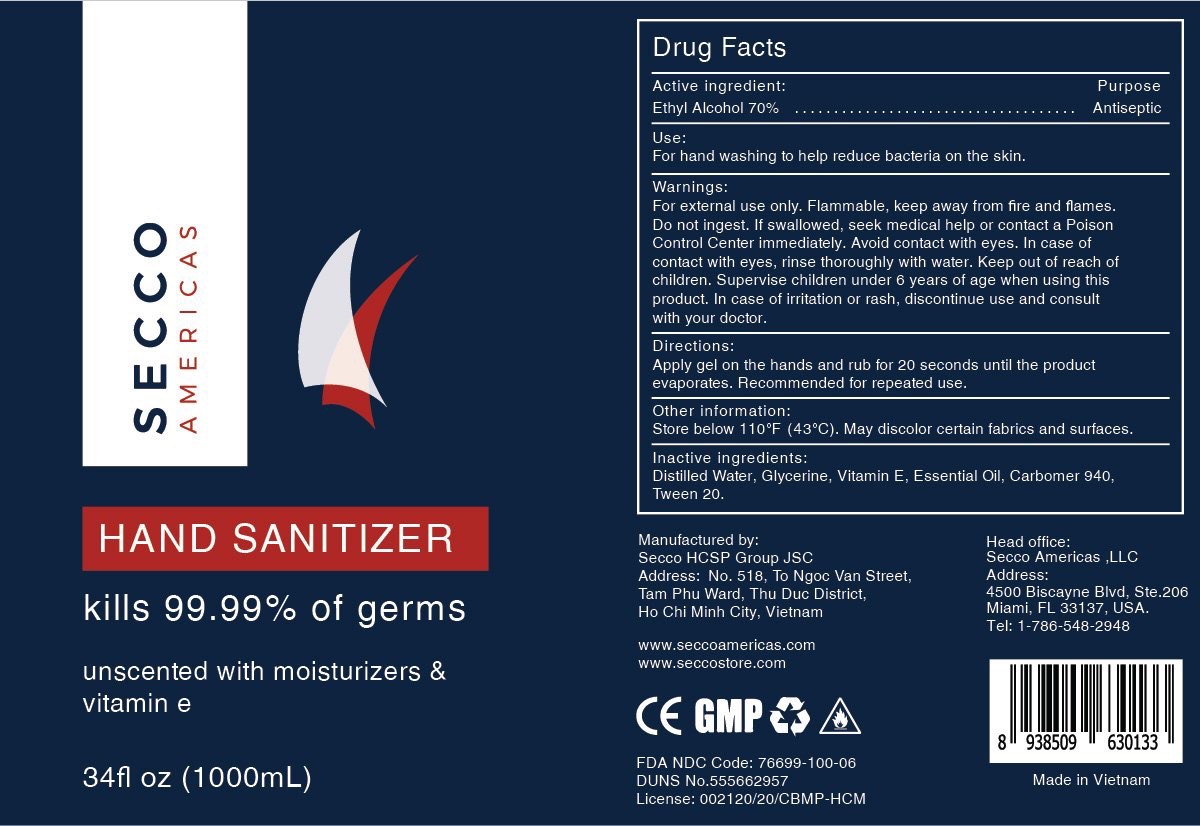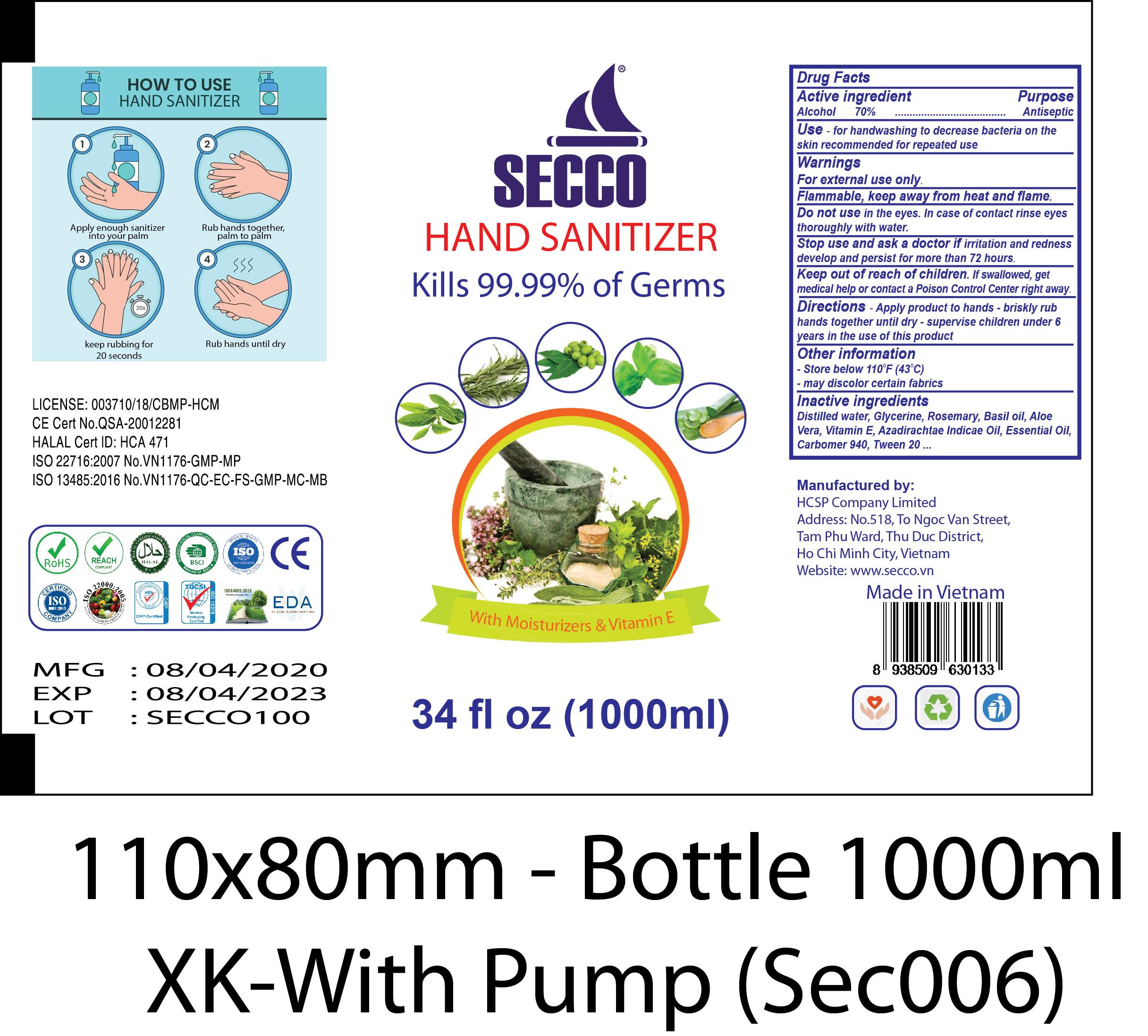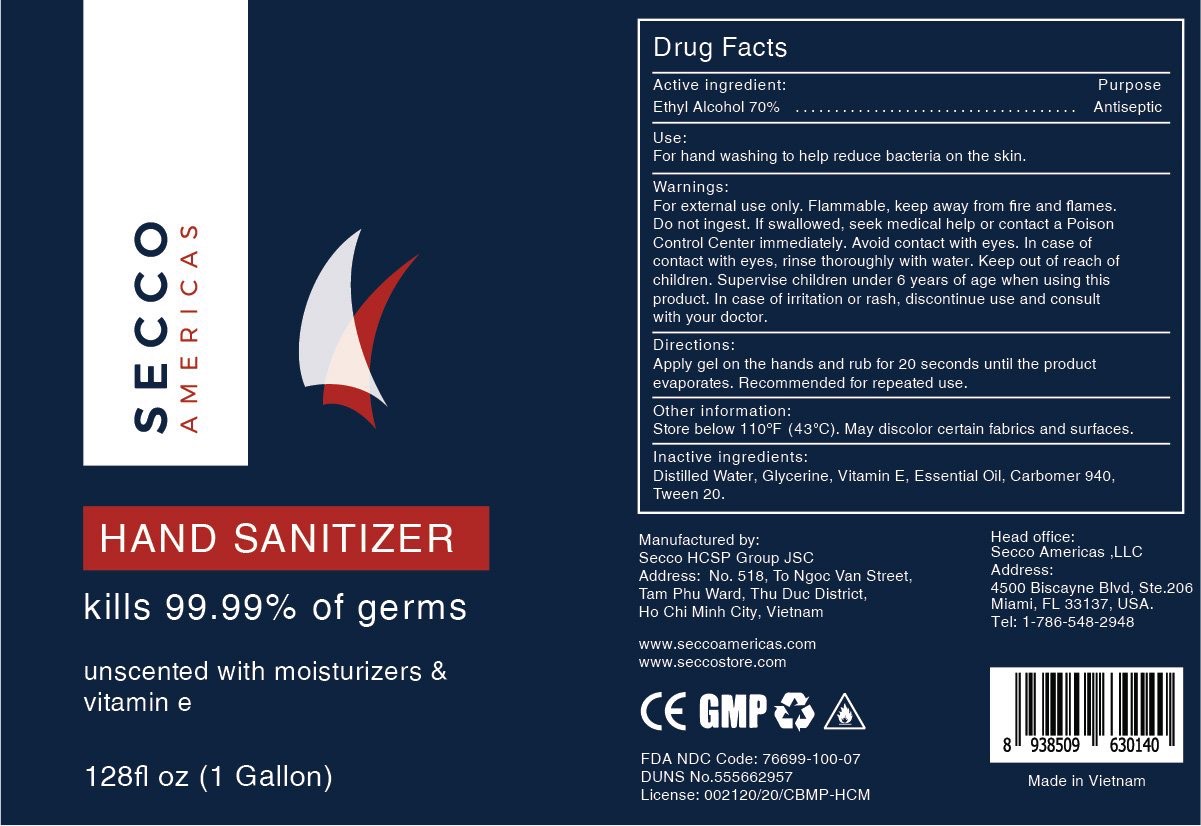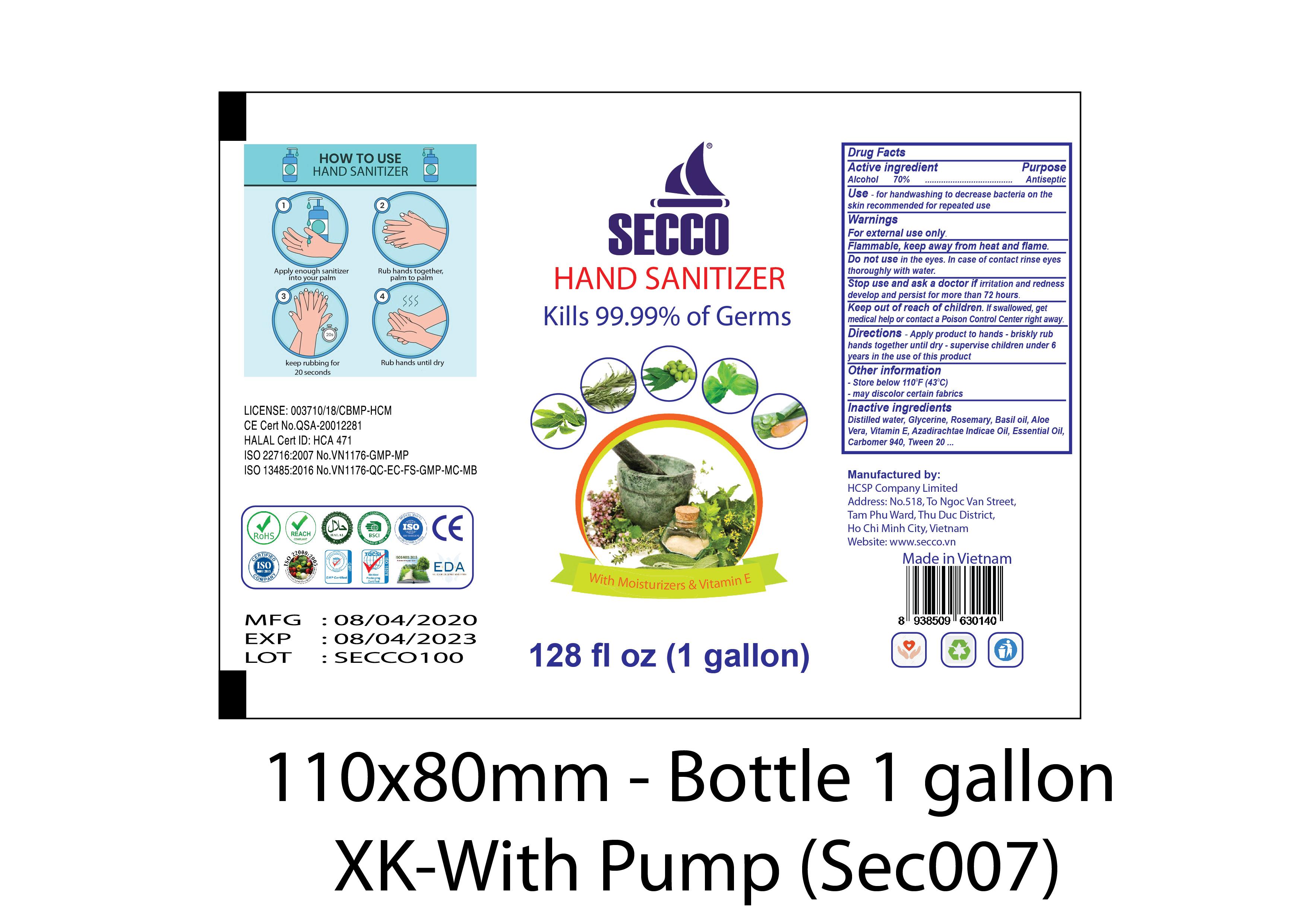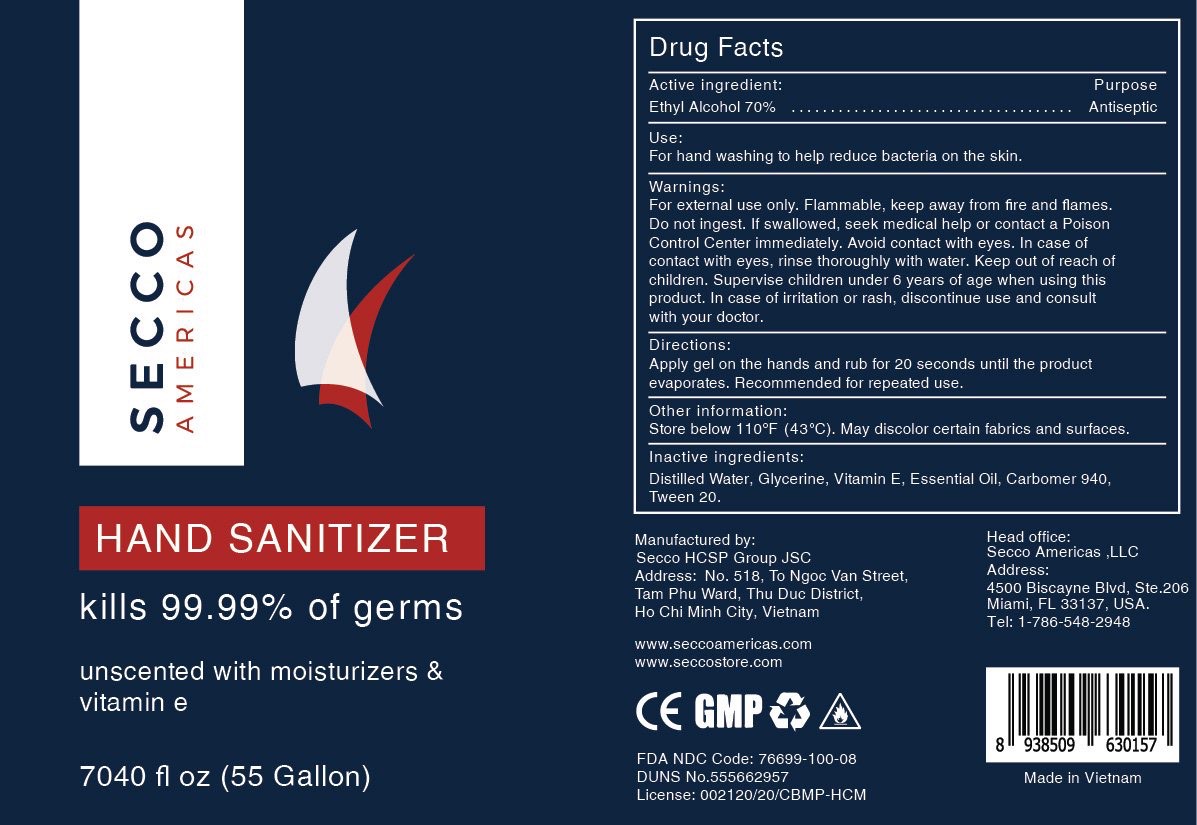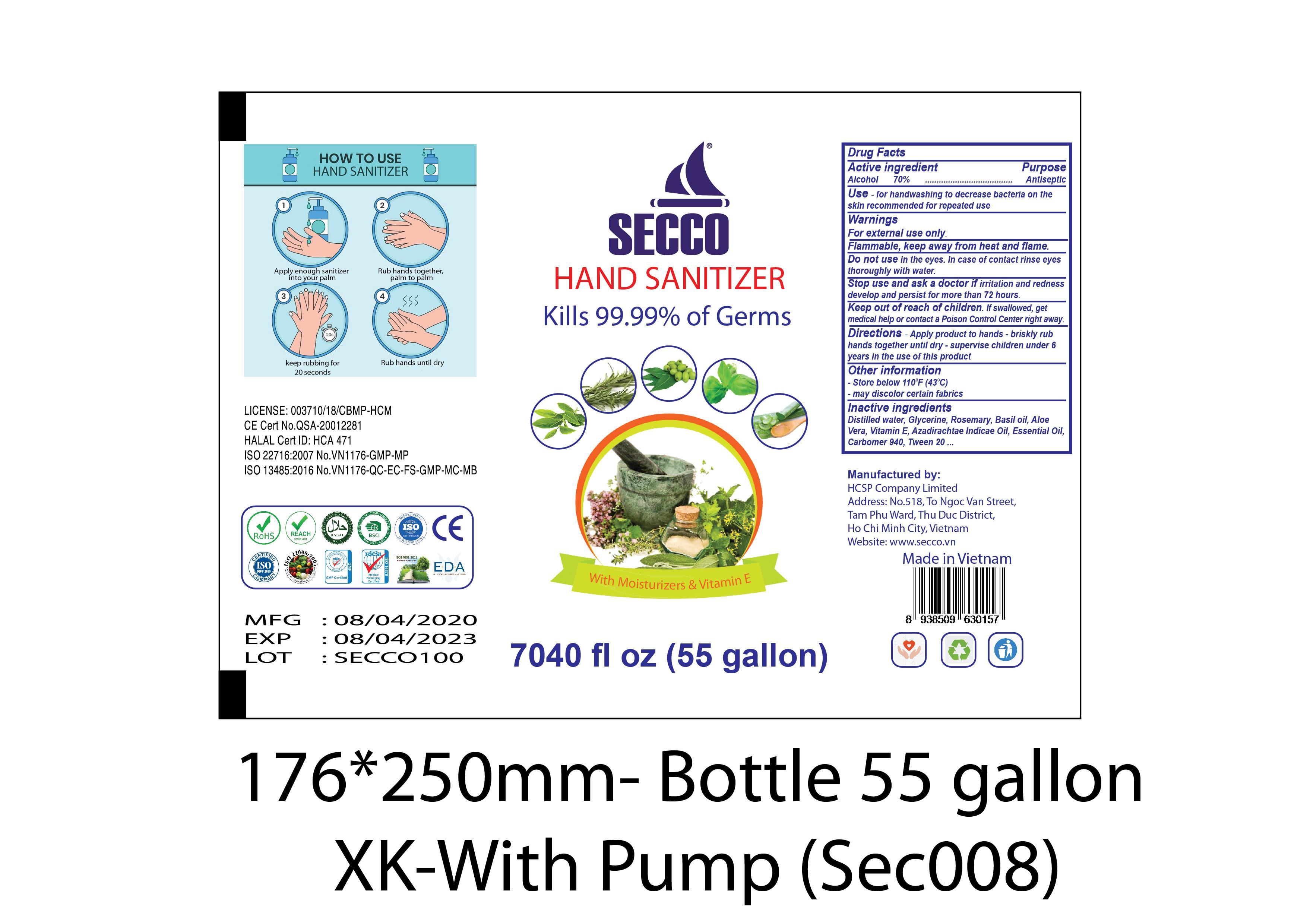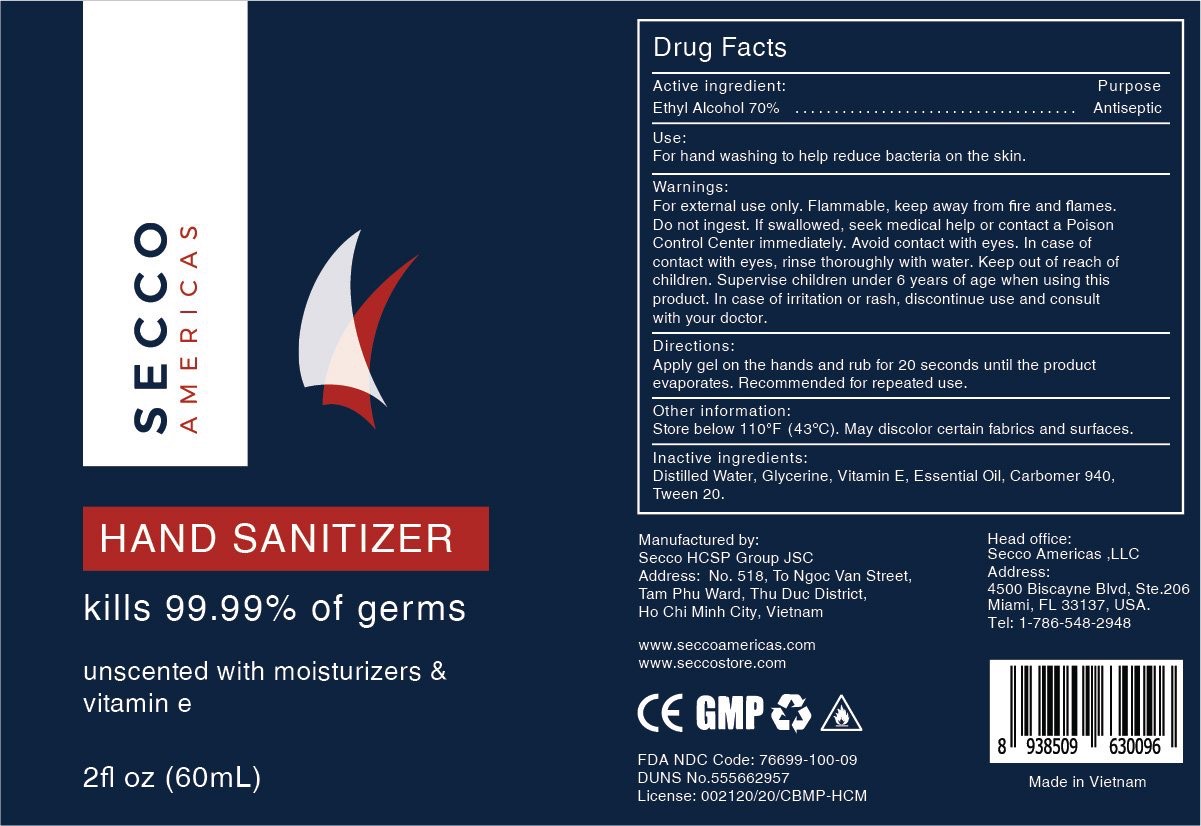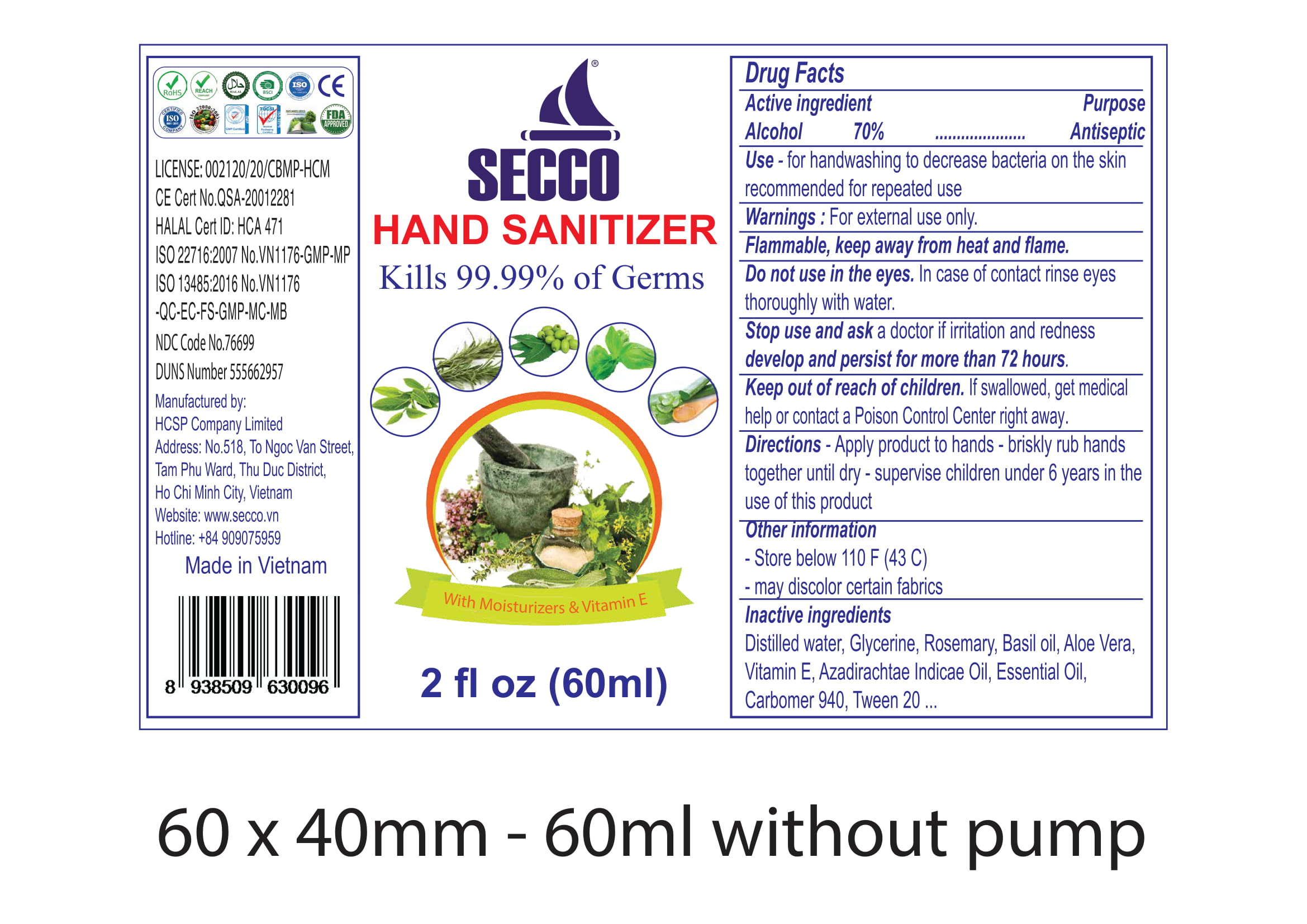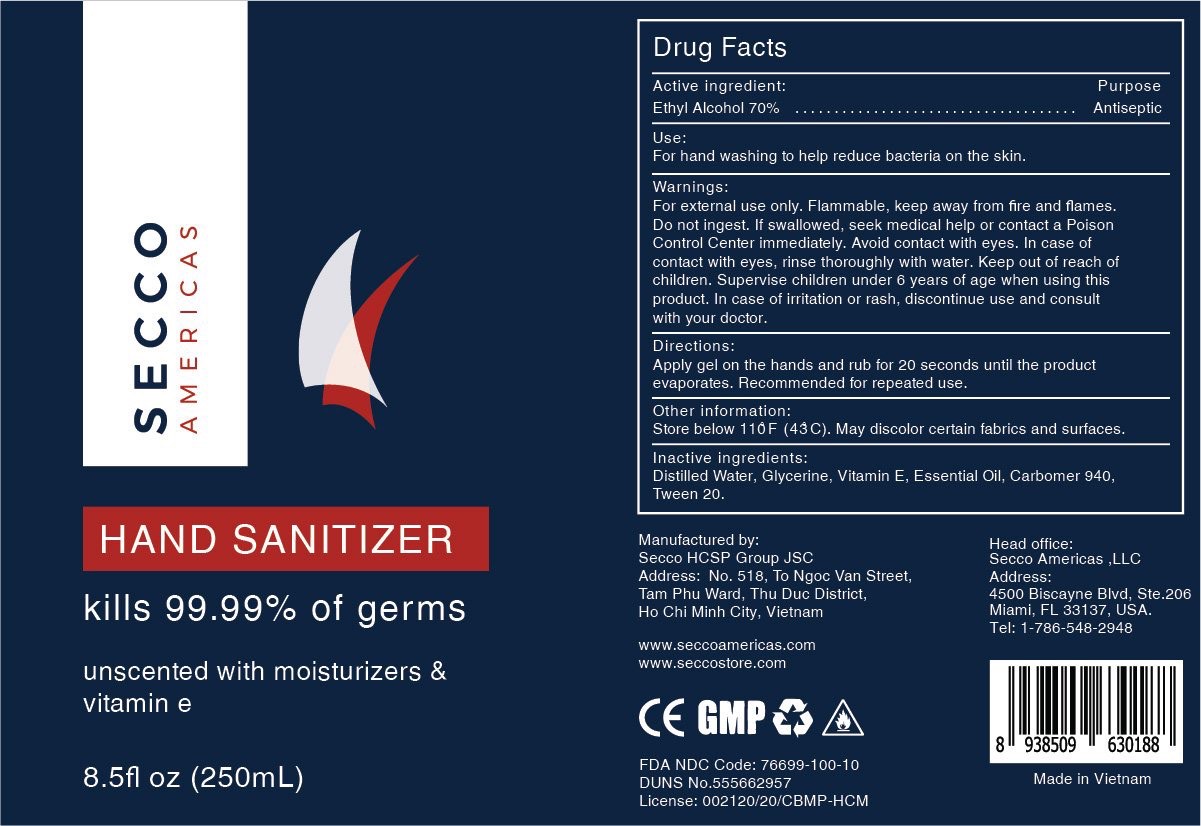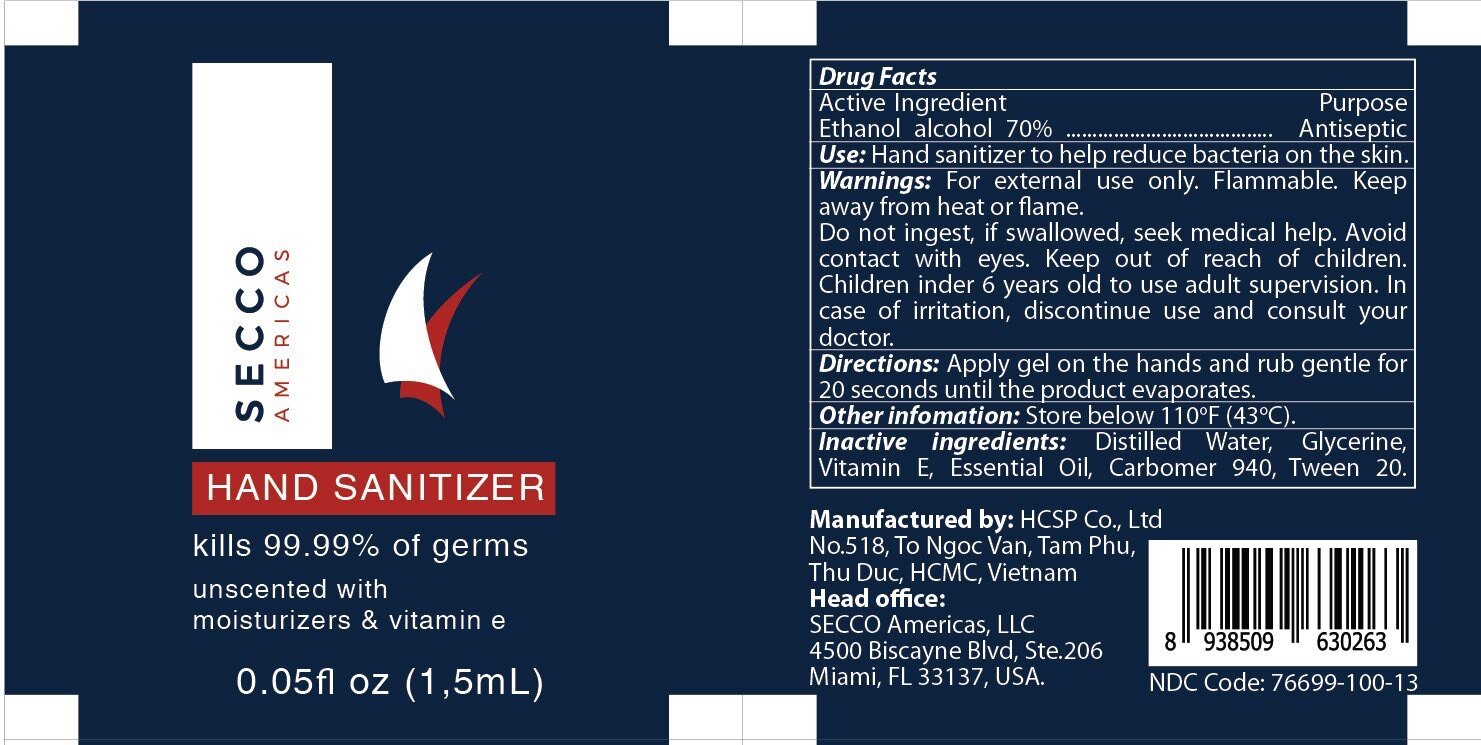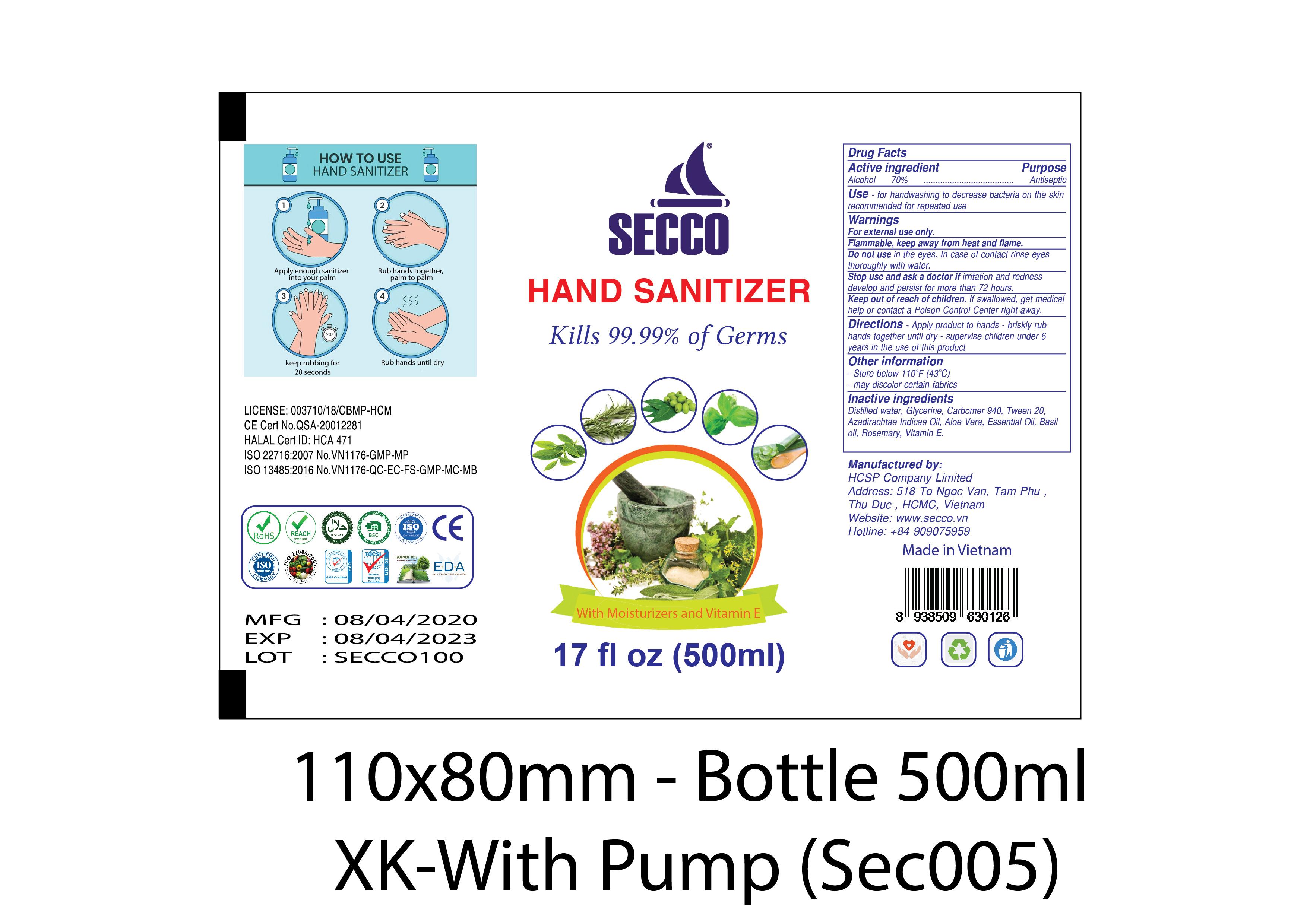 DRUG LABEL: Hand Sanitizer
NDC: 76699-100 | Form: LIQUID
Manufacturer: SECCO HCSP GROUP JSC
Category: otc | Type: HUMAN OTC DRUG LABEL
Date: 20201011

ACTIVE INGREDIENTS: ALCOHOL 70 mL/100 mL
INACTIVE INGREDIENTS: ALOE VERA LEAF 1 mL/100 mL; CAJUPUT OIL 0.5 mL/100 mL; AZADIRACHTA INDICA SEED OIL 0.5 mL/100 mL; ROSEMARY 1.45 mL/100 mL; POLYSORBATE 20 0.1 mL/100 mL; .ALPHA.-TOCOPHEROL ACETATE 0.6 mL/100 mL; BASIL OIL 1.45 mL/100 mL; GLYCERIN 1.45 mL/100 mL; WATER 22.5 mL/100 mL; CARBOMER 940 0.4 mL/100 mL

This is a hand sanitizer manufactured according to the Temporary Policy for Preparation of Certain Alcohol-Based Hand Sanitizer Products During the Public Health Emergency (CoViD-19); Guidance for Industry.

The hand sanitizer is manufactured using only the following United States Pharmacopoeia (USP) grade ingredients in the preparation of the product (percentage in final product formulation) consistent with World Health Organization (WHO) recommendations:

1. Alcohol (ethanol) (USP or Food Chemical Codex (FCC) grade) (80%, volume/volume (v/v)) in an aqueous solution denatured according to Alcohol and Tobacco Tax and Trade Bureau regulations in 27 CFR part 20.
2. Glycerol (1.45% v/v).
3. Hydrogen peroxide (0.125% v/v).
4. Sterile distilled water or boiled cold water.

The firm does not add other active or inactive ingredients. Different or additional ingredients may impact the quality and potency of the product.

Active Ingredient(s)

Alcohol 70% v/v. Purpose: Antiseptic

Purpose

Antiseptic, Hand Sanitizer

Use

For handwashing to decrease bacteria on the skin recommended for repeated use

Warnings

For external use only. Flammable. Keep away from heat or flame

Do not use

- in the eyes. In case of contact rinse eyes thoroughly with water.
- Keep out of reach of children. If swallowed, get medical help and contact a Poison Control Center right away.
- Stop use and ask a doctor if irritation and redness develop and persist for more than 72 hours.

When using this product keep out of eyes, ears, and mouth. In case of contact with eyes, rinse eyes thoroughly with water.
Stop use and ask a doctor if irritation or rash occurs. These may be signs of a serious condition.
Keep out of reach of children. If swallowed, get medical help or contact a Poison Control Center right away.

Stop use and ask a doctor if irritation and redness develop and persist for more than 72 hours.

Keep out of reach of children. If swallowed, get medical help or contact a Poison Control Center right away.

Directions

- Apply enough sanitizer into your palm
- Rub hands together, palm to palm
- Keep rubbing for 20 seconds
- Rub hands until dry
- P

Other information

- Store below 110F (43C)

Inactive ingredients

distilled water, glycerine, carbomer 940, tween 20, azadirachtae indicae oil, aloe vera, essential oil, basil oil, rosemary, vitamin e.

RECENT MAJOR CHANGES

Indications and Usage: for handwashing to decrease bacteria on the skin recommended for repeated use (03-2020)

Dosage and administration: apply enough sanitizer into your palm, rub hands together plam to plam, keep rubbing for 20 seconds, rub hands until dry (03-2020)

Package Label - Principal Display Panel

30ml NDC: 76699-100-03

50mL NDC: 76699-100-04

60mL NDC: 76699-100-09

100 mL NDC: 76699-100-01

300 mL NDC: 76699-100-02

500 mL NDC: 76699-100-05

1000 mL NDC: 76699-100-06

3.85L NDC: 76699-100-07

208L NDC: 76699-100-08

60mL: NDC 76699-100-09

250mL: NDC 76699-100-10

1.5mL: NDC 76699-100-13